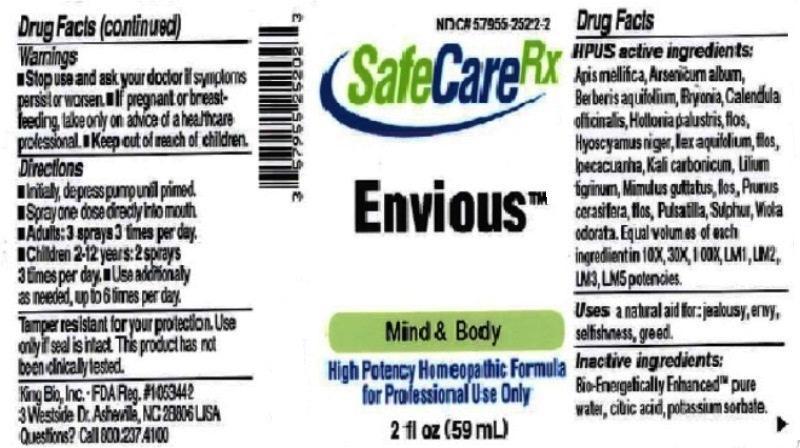 DRUG LABEL: Envious
NDC: 57955-2522 | Form: LIQUID
Manufacturer: King Bio Inc.
Category: homeopathic | Type: HUMAN OTC DRUG LABEL
Date: 20150604

ACTIVE INGREDIENTS: APIS MELLIFERA 10 [hp_X]/59 mL; ARSENIC TRIOXIDE 10 [hp_X]/59 mL; MAHONIA AQUIFOLIUM ROOT BARK 10 [hp_X]/59 mL; BRYONIA ALBA ROOT 10 [hp_X]/59 mL; CALENDULA OFFICINALIS FLOWERING TOP 10 [hp_X]/59 mL; HOTTONIA PALUSTRIS FLOWER 10 [hp_X]/59 mL; HYOSCYAMUS NIGER 10 [hp_X]/59 mL; ILEX AQUIFOLIUM FLOWERING TOP 10 [hp_X]/59 mL; IPECAC 10 [hp_X]/59 mL; POTASSIUM CARBONATE 10 [hp_X]/59 mL; LILIUM LANCIFOLIUM WHOLE FLOWERING 10 [hp_X]/59 mL; MIMULUS GUTTATUS FLOWERING TOP 10 [hp_X]/59 mL; SANDALWOOD OIL 10 [hp_X]/59 mL; PRUNUS CERASIFERA FLOWER 10 [hp_X]/59 mL; PULSATILLA VULGARIS 10 [hp_X]/59 mL; SULFUR 10 [hp_X]/59 mL; VIOLA ODORATA 10 [hp_X]/59 mL
INACTIVE INGREDIENTS: WATER; ANHYDROUS CITRIC ACID; POTASSIUM SORBATE

Envious™

ACTIVE INGREDIENT

Drug Facts__________________________________________________________________________________________________________

HPUS active ingredients: Apis mellifica, Arsenicum album, Berberis aquifolium, Bryonia, Calendula officinalis, Hottonia palustris, flos, Hyoscyamus niger, Ilex aquifolium, flos, Ipecauanha, Kali carbonicum, Lilium tigrinum, Mimulus guttatus, flos, Oleum santali, Prunus cerasifera, flos, Pulsatilla, Sulphur, Viola odorata. Equal volumes of each ingredient in 10X, 30X, 100X, LM1, LM2, LM3 potencies.

INDICATIONS AND USAGE

Uses a natural aid for: jealousy, envy, selfishness, greed.

Inactive Ingredients:

Bio-Energetically Enhanced™ pure water, citric acid and potassium sorbate.

Warnings

- Stop use and ask your doctor if symptoms persist or worsen.
- If pregnant or breast-feeding, take only on advice of a healthcare professional.

- Keep out of reach of children.

Directions

- Initially, depress pump until primed.
- Spray one dose directly into mouth.
- Adults: 3 sprays 3 times per day.
- Children 2-12 years: 2 sprays 3 times per day.
- Use additionally as needed, up to 6 times per day.

OTHER SAFETY INFORMATION

Tamper resistant for your protection. Use only if safety seal is intact. This product has not been clinically tested.

PURPOSE

Uses a natural aid for:

- jealousy
- envy
- selfishness
- greed